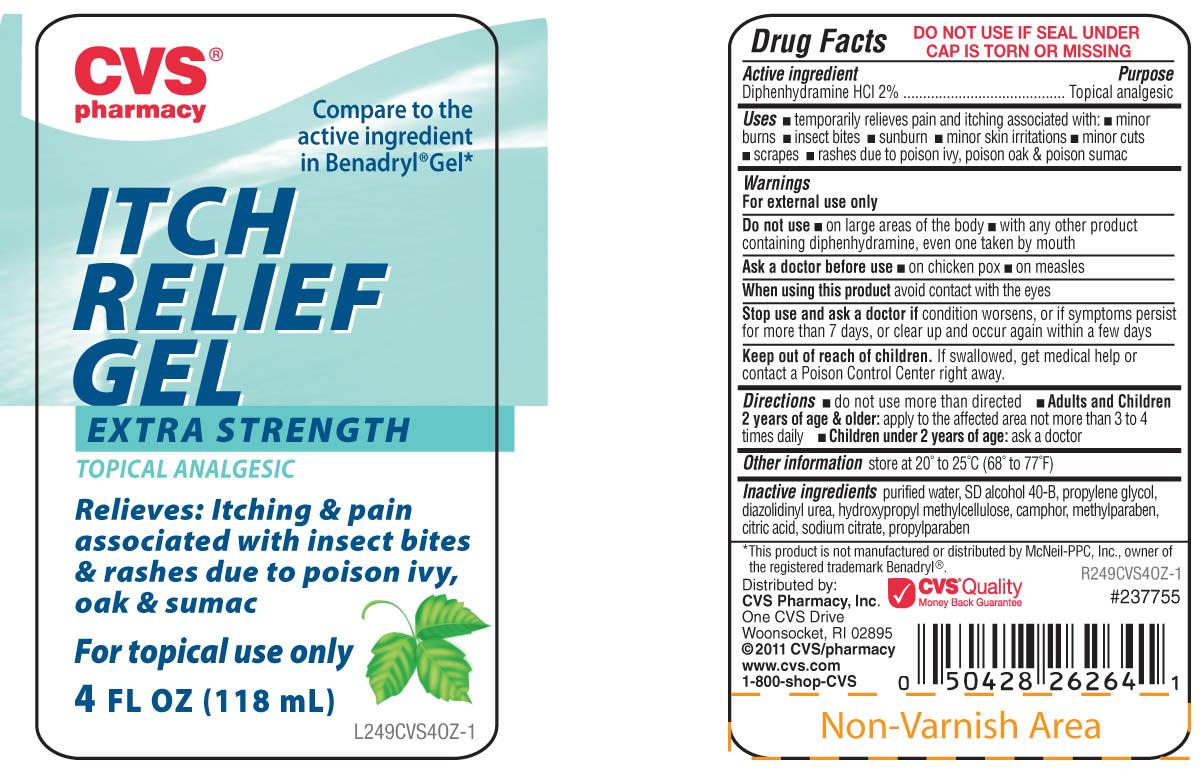 DRUG LABEL: CVS
NDC: 59779-048 | Form: GEL
Manufacturer: CVS Pharmacy
Category: otc | Type: HUMAN OTC DRUG LABEL
Date: 20120427

ACTIVE INGREDIENTS: DIPHENHYDRAMINE HYDROCHLORIDE 20.5 mg/1 mL
INACTIVE INGREDIENTS: WATER; ALCOHOL; PROPYLENE GLYCOL; DIAZOLIDINYL UREA; METHYLPARABEN; PROPYLPARABEN; ANHYDROUS CITRIC ACID; CAMPHOR (SYNTHETIC); SODIUM CITRATE; HYPROMELLOSE 2910 (4000 MPA.S); GLYCERIN

DRUG FACTS

Active ingredient Purpose
Diphenhydramine HCL 2% ...................................................................Topical analgesic

Uses
Temporarily relieves pain and itching associated with
- minor burns - insect bites - sunburn - minor skin irritations
- minor cuts - scrapes - rashes due to poison ivy, poison oak and poison sumac

Keep out of reach of children. If swallowed, get medical help or contact a
Poison Control Center right away.

Uses
Temporarily relieves pain and itching associated with
- minor burns - insect bites - sunburn - minor skin irritations
- minor cuts - scrapes - rashes due to poison ivy, poison oak and poison sumac

Warnings
For external use only
Do not use - on large areas of the body
- with any other product containing diphenhydramine,
even one taken by mouth
Ask a doctor before use - on chicken pox - on measles
When using this product avoid contact with the eyes
Stop use and ask a doctor if condition worsens,
or if the symptoms persist for more than 7 days
or clear up and occur again within a few days.
Keep out of reach of children. If swallowed, get medical help or contact a Poison Control Center right away.

Directions
- do not use more than directed
- Adults and children 2 years and older: apply to affected area not more than 3 to 4 times daily
- Children under 2 years of age: ask a doctor
Other information
Store at 20 degrees to 25 degrees C (68 degrees to 77 degrees F)

Inactive Ingredients
purified water, SD alcohol 40-B, propylene glycol, diazolidinyl urea, hydroxypropyl methylcellolose, camphor, methylparaben, citric acid, sodium citrate, propylparaben